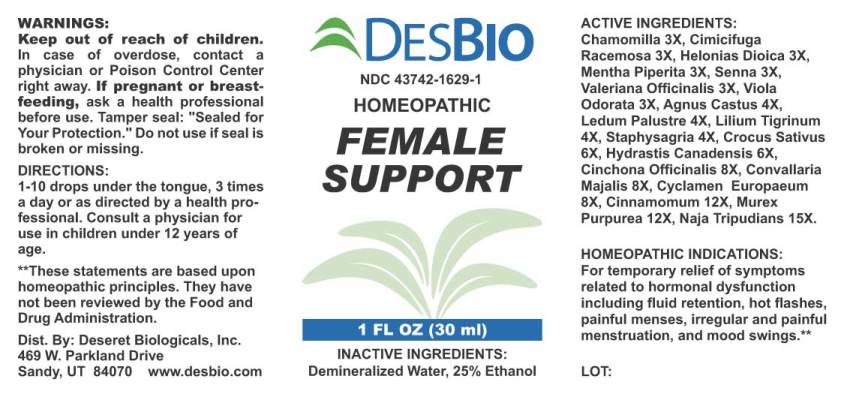 DRUG LABEL: Female Support
NDC: 43742-1629 | Form: LIQUID
Manufacturer: Deseret Biologicals, Inc.
Category: homeopathic | Type: HUMAN PRESCRIPTION DRUG LABEL
Date: 20210628

ACTIVE INGREDIENTS: MATRICARIA RECUTITA 3 [hp_X]/1 mL; BLACK COHOSH 3 [hp_X]/1 mL; CHAMAELIRIUM LUTEUM ROOT 3 [hp_X]/1 mL; MENTHA PIPERITA 3 [hp_X]/1 mL; SENNA LEAF 3 [hp_X]/1 mL; VALERIAN 3 [hp_X]/1 mL; VIOLA ODORATA 3 [hp_X]/1 mL; CHASTE TREE FRUIT 4 [hp_X]/1 mL; LEDUM PALUSTRE TWIG 4 [hp_X]/1 mL; LILIUM LANCIFOLIUM WHOLE FLOWERING 4 [hp_X]/1 mL; DELPHINIUM STAPHISAGRIA SEED 4 [hp_X]/1 mL; SAFFRON 6 [hp_X]/1 mL; GOLDENSEAL 6 [hp_X]/1 mL; CINCHONA OFFICINALIS BARK 8 [hp_X]/1 mL; CONVALLARIA MAJALIS 8 [hp_X]/1 mL; CYCLAMEN PURPURASCENS TUBER 8 [hp_X]/1 mL; CINNAMON 12 [hp_X]/1 mL; HEXAPLEX TRUNCULUS HYPOBRANCHIAL GLAND JUICE 12 [hp_X]/1 mL; NAJA NAJA VENOM 15 [hp_X]/1 mL
INACTIVE INGREDIENTS: WATER; ALCOHOL

Drug Facts:

ACTIVE INGREDIENTS:

Chamomilla 3X, Cimicifuga Racemosa 3X, Helonias Dioica 3X, Mentha Piperita 3X, Senna (Cassia Angustifolia) 3X, Valeriana Officinalis 3X, Viola Odorata 3X, Agnus Castus 4X, Ledum Palustre 4X, Lilium Tigrinum 4X, Staphysagria 4X, Crocus Sativus 6X, Hydrastis Canadensis 6X, Cinchona Officinalis 8X, Convallaria Majalis 8X, Cyclamen Europaeum 8X, Cinnamomum 12X, Murex Purpurea 12X, Naja Tripudians 15X.

HOMEOPATHIC INDICATIONS:

For temporary relief of symptoms related to hormonal dysfunction including fluid retention, hot flashes, painful menses, irregular and painful menstruation, and mood swings.**

** These statements are based upon homeopathic principles. They have not been reviewed by the Food and Drug Administration.

WARNINGS:

Keep out of reach of children. In case of overdose, contact a physician or Poison Control Center right away.

If pregnant or breast-feeding, ask a health professional before use.

Tamper seal: "Sealed for Your Protection." Do not use if seal is broken or missing.

Keep out of reach of children. In case of overdose, contact a physician or Poison Control Center right away.

DIRECTIONS:

1-10 drops under the tongue, 3 times a day or as directed by a health professional. Consult a physician for use in children under 12 years of age.

HOMEOPATHIC INDICATIONS:

For temporary relief of symptoms related to hormonal dysfunction including fluid retention, hot flashes, painful menses, irregular and painful menstruation, and mood swings.**

** These statements are based upon homeopathic principles. They have not been reviewed by the Food and Drug Administration.

INACTIVE INGREDIENTS:

Demineralized Water, 25% Ethanol

QUESTIONS:

Dist. By: Deseret Biologicals, Inc.

469 W. Parkland Drive

Sandy, UT 84070 www.desbio.com

PACKAGE LABEL DISPLAY:

DESBIO

NDC 43742-1629-1

HOMEOPATHIC

FEMALE

SUPPORT

1 FL OZ (30ml)